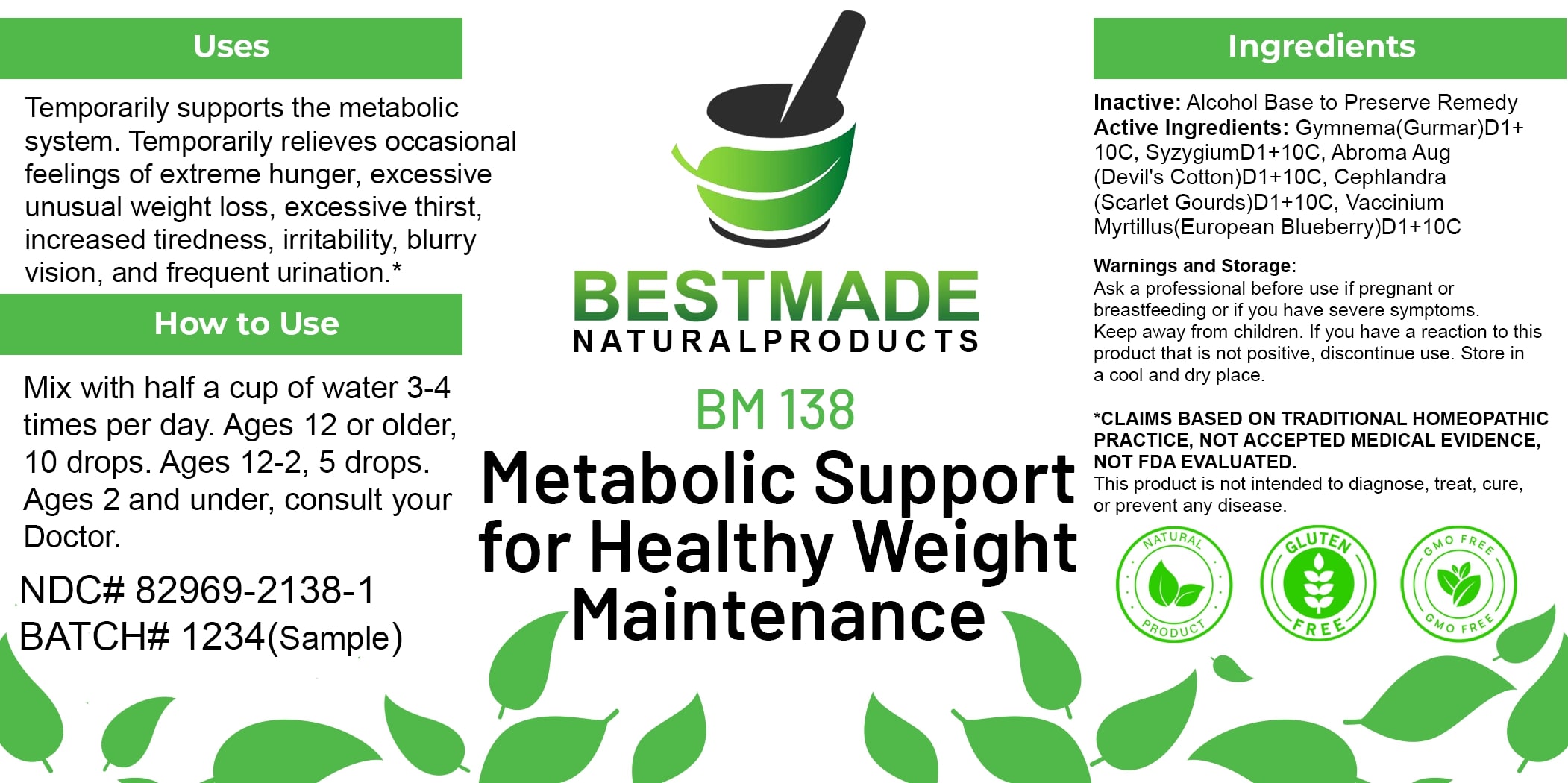 DRUG LABEL: Bestmade Natural Products BM138
NDC: 82969-2138 | Form: LIQUID
Manufacturer: Bestmade Natural Products
Category: homeopathic | Type: HUMAN OTC DRUG LABEL
Date: 20250214

ACTIVE INGREDIENTS: ABROMA AUGUSTUM WHOLE 10 [hp_C]/10 [hp_C]; BILBERRY 10 [hp_C]/10 [hp_C]; GYMNEMA SYLVESTRE WHOLE 10 [hp_C]/10 [hp_C]; COCCINIA GRANDIS WHOLE 10 [hp_C]/10 [hp_C]; SYZYGIUM CUMINI SEED 10 [hp_C]/10 [hp_C]
INACTIVE INGREDIENTS: ALCOHOL 10 [hp_C]/10 [hp_C]

BM138

DOSAGE AND ADMINISTRATION

How to Use

Mix with half a cup of water 3-4 times per day. Ages 12 or older, 10 drops. Ages 12-2, 5 drops. Ages 2 and under, consult your Doctor.

INACTIVE INGREDIENT

Ingredients

Inactive: Alcohol Base to Preserve Remedy

ACTIVE INGREDIENT

Active Ingredients: Gymnema(Gurmar)D1+ 10C, SyzygiumD1+10C, Abroma Aug (Devil's Cotton)D1+10C, Cephlandra Scarlet Gourds D1+10C, Vaccinium Myrtillus(European Blueberry)D1+10C

Uses

Temporarily supports the metabolic system. Temporarily relieves occasional feelings of extreme hunger, excessive unusual weight loss, excessive thirst, increased tiredness, irritability, blurry vision, and frequent urination.*

*CLAIMS BASED ON TRADITIONAL HOMEOPATHIC PRACTICE, NOT ACCEPTED MEDICAL EVIDENCE. NOT FDA EVALUATED.

This product is not intended to diagnose, treat, cure, or prevent any disease.

Uses

Temporarily supports the metabolic system. Temporarily relieves occasional feelings of extreme hunger, excessive unusual weight loss, excessive thirst, increased tiredness, irritability, blurry vision, and frequent urination.*

*CLAIMS BASED ON TRADITIONAL HOMEOPATHIC PRACTICE, NOT ACCEPTED MEDICAL EVIDENCE. NOT FDA EVALUATED.

This product is not intended to diagnose, treat, cure, or prevent any disease.

KEEP OUT OF REACH OF CHILDREN

Warnings and Storage:

Ask a professional before use if pregnant or breastfeeding or if you have severe symptoms. Keep away from children. If you have a reaction to this product that is not positive, discontinue use. Store in a cool and dry place.

Warnings and Storage:

Ask a professional before use if pregnant or breastfeeding or if you have severe symptoms. Keep away from children. If you have a reaction to this product that is not positive, discontinue use. Store in a cool and dry place.

*CLAIMS BASED ON TRADITIONAL HOMEOPATHIC PRACTICE, NOT ACCEPTED MEDICAL EVIDENCE. NOT FDA EVALUATED.

This product is not intended to diagnose, treat, cure, or prevent any disease.

Entire package label